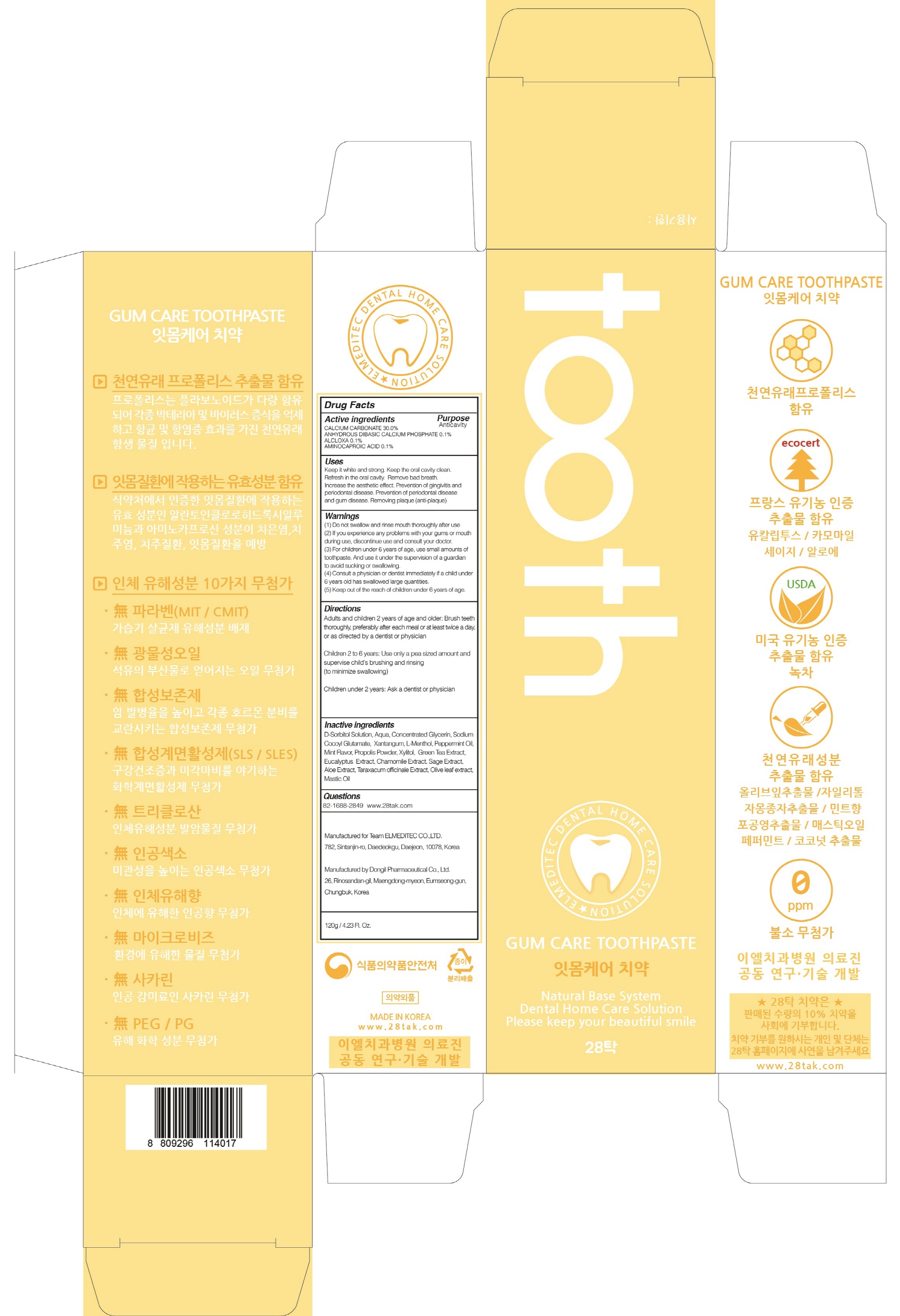 DRUG LABEL: 28TAK GUM CARE TOOTH
NDC: 72440-030 | Form: PASTE, DENTIFRICE
Manufacturer: ELMEDITEC CO.,LTD
Category: otc | Type: HUMAN OTC DRUG LABEL
Date: 20180717

ACTIVE INGREDIENTS: CALCIUM CARBONATE 36.0 g/120 g; ANHYDROUS DIBASIC CALCIUM PHOSPHATE 0.12 g/120 g; ALCLOXA 0.12 g/120 g; AMINOCAPROIC ACID 0.12 g/120 g
INACTIVE INGREDIENTS: Water; Xylitol

ACTIVE INGREDIENT

Active ingredients: CALCIUM CARBONATE 30.0%, ANHYDROUS DIBASIC CALCIUM PHOSPHATE 0.1%, ALCLOXA 0.1%, AMINOCAPROIC ACID 0.1%

INACTIVE INGREDIENT

Inactive ingredients:

D-Sorbitol Solution, Aqua, Concentrated Glycerin, Sodium Cocoyl Glutamate, Xantangum, L-Menthol, Peppermint Oil, Mint Flavor, Propolis Powder, Xylitol, Green Tea Extract, Eucalyptus Extract, Chamomile Extract, Sage Extract, Aloe Extract, Taraxacum officinale Extract, Olive leaf extract, Mastic Oil

PURPOSE

Purpose: Anticavity

WARNINGS

(1) Do not swallow and rinse mouth thoroughly after use (2) If you experience any problems with your gums or mouth during use, discontinue use and consult your doctor. (3) For children under 6 years of age, use small amounts of toothpaste. And use it under the supervision of a guardian to avoid sucking or swallowing. (4) Consult a physician or dentist immediately if a child under 6 years old has swallowed large quantities. (5) Keep out of the reach of children under 6 years of age.

KEEP OUT OF REACH OF CHILDREN

Keep out of the reach of children under 6 years of age.

Uses

Keep your teeth white and strong. Keep your mouth clean. Refresh the inside of the mouth. To prevent tooth decay and remove bad breath. Increase esthetic effect. Removal of plaque (anti-plaque)

Directions

Adults and children 2 years of age and older: Brush teeth thoroughly, preferably after each meal or at least twice a day, or as directed by a dentist or physician

Children 2 to 6 years: Use only a pea sized amount and supervise child's brushing and rinsing (to minimize swallowing)

Children under 2 years: Ask a dentist or physician